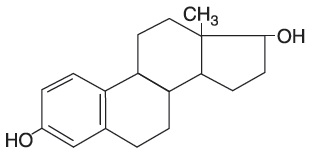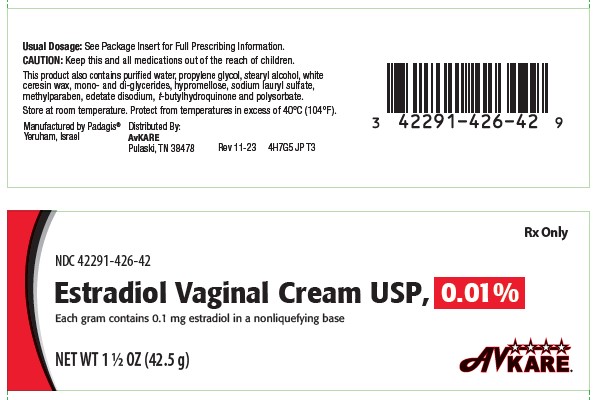 DRUG LABEL: Estradiol Vaginal
NDC: 42291-426 | Form: CREAM
Manufacturer: AvKARE
Category: prescription | Type: HUMAN PRESCRIPTION DRUG LABEL
Date: 20260114

ACTIVE INGREDIENTS: ESTRADIOL 0.1 mg/1 g
INACTIVE INGREDIENTS: WATER; PROPYLENE GLYCOL; STEARYL ALCOHOL; CERESIN; HYPROMELLOSE 2208 (4000 MPA.S); SODIUM LAURYL SULFATE; METHYLPARABEN; EDETATE DISODIUM; TERT-BUTYLHYDROQUINONE; POLYSORBATE 80; GLYCERYL MONOSTEARATE

Estradiol Vaginal Cream USP, 0.01%

Rx Only

WARNING: ENDOMETRIAL CANCER, CARDIOVASCULAR DISORDERS, BREAST CANCER and PROBABLE DEMENTIA

Estrogen-Alone Therapy

Endometrial Cancer

There is an increased risk of endometrial cancer in a woman with a uterus who uses unopposed estrogens. Adding a progestin to estrogen therapy has been shown to reduce the risk of endometrial hyperplasia, which may be a precursor to endometrial cancer. Adequate diagnostic measures, including directed or random endometrial sampling when indicated, should be undertaken to rule out malignancy in postmenopausal women with undiagnosed persistent or recurring abnormal genital bleeding [see WARNINGS, Malignant Neoplasms, Endometrial Cancer].

Cardiovascular Disorders and Probable Dementia

Estrogen-alone therapy should not be used for the prevention of cardiovascular disease or dementia [see CLINICAL STUDIES and WARNINGS, Cardiovascular Disorders, and Probable Dementia].

The Women’s Health Initiative (WHI) estrogen-alone substudy reported increased risks of stroke and deep vein thrombosis (DVT) in postmenopausal women (50 to 79 years of age) during 7.1 years of treatment with daily oral conjugated estrogens (CE) [0.625 mg]-alone, relative to placebo [see CLINICAL STUDIES and WARNINGS, Cardiovascular Disorders].

The WHI Memory Study (WHIMS) estrogen-alone ancillary study of WHI reported an increased risk of developing probable dementia in postmenopausal women 65 years of age or older during 5.2 years of treatment with daily CE (0.625 mg) -alone, relative to placebo. It is unknown whether this finding applies to younger postmenopausal women [see CLINICAL STUDIES and WARNINGS, Probable Dementia and PRECAUTIONS, Geriatric Use].

In the absence of comparable data, these risks should be assumed to be similar for other doses of CE and other dosage forms of estrogens.

Estrogens with or without progestins should be prescribed at the lowest effective doses and for the shortest duration consistent with treatment goals and risks for the individual woman.

Estrogen Plus Progestin Therapy

Cardiovascular Disorders and Probable Dementia

Estrogen plus progestin therapy should not be used for the prevention of cardiovascular disease or dementia [see CLINICAL STUDIES and WARNINGS, Cardiovascular Disorders, and Probable Dementia].

The WHI estrogen plus progestin substudy reported increased risks of DVT, pulmonary embolism (PE), stroke and myocardial infarction (MI) in postmenopausal women (50 to 79 years of age) during 5.6 years of treatment with daily oral CE (0.625 mg) combined with medroxyprogesterone acetate (MPA) [2.5 mg], relative to placebo [see CLINICAL STUDIES and WARNINGS, Cardiovascular Disorders].

The WHIMS estrogen plus progestin ancillary study of the WHI reported an increased risk of developing probable dementia in postmenopausal women 65 years of age or older during 4 years of treatment with daily CE (0.625 mg) combined with MPA (2.5 mg), relative to placebo. It is unknown whether this finding applies to younger postmenopausal women [see CLINICAL STUDIES and WARNINGS, Probable Dementia and PRECAUTIONS, Geriatric Use].

Breast Cancer

The WHI estrogen plus progestin substudy also demonstrated an increased risk of invasive breast cancer [see CLINICAL STUDIES and WARNINGS, Malignant Neoplasms, Breast Cancer].

In the absence of comparable data, these risks should be assumed to be similar for other doses of CE and MPA, and other combinations and dosage forms of estrogens and progestins.

Estrogens with or without progestins should be prescribed at the lowest effective doses and for the shortest duration consistent with treatment goals and risks for the individual woman.

DESCRIPTION

Each gram of Estradiol Vaginal Cream USP, 0.01% contains 0.1 mg estradiol in a nonliquefying base containing purified water, propylene glycol, stearyl alcohol, white ceresin wax, mono- and di-glycerides, hypromellose 2208 (4000 cps), sodium lauryl sulfate, methylparaben, edetate di-sodium, tertiary-butylhydroquinone and polysorbate 80.

Estradiol is chemically described as estra-1,3,5(10)-triene-3, 17(beta)-diol. It has an empirical formula of C18H24O2 and molecular weight of 272.37.

The structural formula is:

CLINICAL PHARMACOLOGY

Endogenous estrogens are largely responsible for the development and maintenance of the female reproductive system and secondary sexual characteristics. Although circulating estrogens exist in a dynamic equilibrium of metabolic interconversions, estradiol is the principal intracellular human estrogen and is substantially more potent than its metabolites, estrone and estriol at the receptor level.

The primary source of estrogen in normally cycling adult women is the ovarian follicle, which secretes 70 to 500 mcg of estradiol daily, depending on the phase of the menstrual cycle. After menopause, most endogenous estrogen is produced by conversion of androstenedione, secreted by the adrenal cortex, to estrone by peripheral tissues. Thus, estrone and the sulfate conjugated form, estrone sulfate, are the most abundant circulating estrogens in postmenopausal women.

Estrogens act through binding to nuclear receptors in estrogen-responsive tissues. To date, two estrogen receptors have been identified. These vary in proportion from tissue to tissue.

Circulating estrogens modulate the pituitary secretion of the gonadotropins, luteinizing hormone (LH) and follicle stimulating hormone (FSH), through a negative feedback mechanism. Estrogens act to reduce the elevated levels of these hormones seen in postmenopausal women.

Pharmacokinetics

Absorption

Estrogen drug products are absorbed through the skin, mucous membranes, and the gastrointestinal tract after release from the drug formulation.

Distribution

The distribution of exogenous estrogens is similar to that of endogenous estrogens. Estrogens are widely distributed in the body and are generally found in higher concentrations in the sex hormone target organs. Estrogens circulate in the blood largely bound to sex hormone binding globulin (SHBG) and albumin.

Metabolism

Exogenous estrogens are metabolized in the same manner as endogenous estrogens. Circulating estrogens exist in a dynamic equilibrium of metabolic interconversions. These transformations take place mainly in the liver. Estradiol is converted reversibly to estrone, and both can be converted to estriol, which is the major urinary metabolite. Estrogens also undergo enterohepatic recirculation via sulfate and glucuronide conjugation in the liver, biliary secretion of conjugates into the intestine, and hydrolysis in the gut followed by reabsorption. In postmenopausal women, a significant proportion of the circulating estrogens exist as sulfate conjugates, especially estrone sulfate, which serves as a circulating reservoir for the formation of more active estrogens.

Excretion

Estradiol, estrone, and estriol are excreted in the urine along with glucuronide and sulfate conjugates.

Special Populations

No pharmacokinetic studies were conducted in special populations, including patients with renal or hepatic impairment.

Drug Interactions

In vitro and in vivo studies have shown that estrogens are metabolized partially by cytochrome P450 3A4 (CYP3A4). Therefore, inducers or inhibitors of CYP3A4 may affect estrogen drug metabolism. Inducers of CYP3A4 such as St. John’s Wort preparations (Hypericum perforatum), phenobarbital, carbamazepine, and rifampin may reduce plasma concentrations of estrogens, possibly resulting in a decrease in therapeutic effects and/or changes in the uterine bleeding profile. Inhibitors of CYP3A4 such as erythromycin, clarithromycin, ketoconazole, itraconazole, ritonavir and grapefruit juice may increase plasma concentrations of estrogens and may result in side effects.

CLINICAL STUDIES

Women’s Health Initiative Studies

The WHI enrolled approximately 27,000 predominantly healthy postmenopausal women in two substudies to assess the risks and benefits of daily oral CE (0.625 mg)-alone or in combination with MPA (2.5 mg) compared to placebo in the prevention of certain chronic diseases. The primary endpoint was the incidence of coronary heart disease (CHD) (defined as nonfatal MI, silent MI and CHD death), with invasive breast cancer as the primary adverse outcome. A “global index” included the earliest occurrence of CHD, invasive breast cancer, stroke, PE, endometrial cancer (only in the CE plus MPA substudy), colorectal cancer, hip fracture, or death due to other cause. These substudies did not evaluate the effects of CE or CE plus MPA on menopausal symptoms.

WHI Estrogen-Alone Substudy

The WHI estrogen-alone substudy was stopped early because an increased risk of stroke was observed, and it was deemed that no further information would be obtained regarding the risks and benefits of estrogen-alone in predetermined primary endpoints.

Results of the estrogen-alone substudy, which included 10,739 women (average 63 years of age, range 50 to 79; 75.3 percent White, 15.1 percent Black, 6.1 percent Hispanic, 3.6 percent Other), after an average follow-up of 7.1 years are presented in Table 1.

TABLE 1 - Relative and Absolute Risk Seen in the Estrogen-Alone Substudy of WHIa
Event | Relative Risk; CE vs. Placebo; (95% nCIb) | CE; n = 5,310 | Placebo; n = 5,429
Event | Relative Risk; CE vs. Placebo; (95% nCIb) | Absolute Risk per 10,000 Women-Years
CHD eventsc | 0.95 (0.78-1.16) | 54 | 57
Non-fatal MIc | 0.91 (0.73-1.14) | 40 | 43
CHD deathc | 1.01 (0.71-1.43) | 16 | 16
All Strokec | 1.33 (1.15-1.68) | 45 | 33
Ischemic strokec | 1.55 (1.19-2.01) | 38 | 25
Deep vein thrombosisc,d | 1.47 (1.06-2.06) | 23 | 15
Pulmonary embolismc | 1.37 (0.90-2.07) | 14 | 10
Invasive breast cancerc | 0.80 (0.62-1.04) | 28 | 34
Colorectal cancerc | 1.08 (0.75-1.55) | 17 | 16
Hip fracturec | 0.65 (0.45-0.94) | 12 | 19
Vertebral fracturesc,d | 0.64 (0.44-0.93) | 11 | 18
Lower arm/wrist fracturesc,d | 0.58 (0.47-0.72) | 35 | 59
Total fracturesc,d | 0.71 (0.64-0.80) | 144 | 197
Death due to other causese,f | 1.08 (0.88-1.32) | 53 | 50
Overall mortalityc,d | 1.04 (0.88-1.22) | 79 | 75
Global indexg | 1.02 (0.92-1.13) | 206 | 201

a Adapted from numerous WHI publications. WHI publications can be viewed at www.nhlbi.nih.gov/whi.

b Nominal confidence intervals unadjusted for multiple looks and multiple comparisons.

c Results are based on centrally adjudicated data for an average follow-up of 7.1 years.

d Not included in “global index”.

e Results are based on an average follow-up of 6.8 years.

f All deaths, except from breast or colorectal cancer, definite or probable CHD, PE or cerebrovascular disease.

g A subset of the events was combined in a ‘global index” defined as the earliest occurrence of CHD events, invasive breast cancer, stroke, pulmonary embolism, endometrial cancer, colorectal cancer, hip fracture, or death due to other causes.

For those outcomes included in the WHI "global index" that reached statistical significance, the absolute excess risk per 10,000 women-years in the group treated with CE-alone was 12 more strokes, while the absolute risk reduction per 10,000 women-years was 7 fewer hip fractures1. The absolute excess risk of events included in the "global index" was a non-significant 5 events per 10,000 women-years. There was no difference between the groups in terms of all-cause mortality.

No overall difference for primary CHD events (nonfatal MI, silent MI and CHD death) and invasive breast cancer incidence in women receiving CE-alone compared with placebo was reported in final centrally adjudicated results from the estrogen-alone substudy, after an average follow-up of 7.1 years.

Centrally adjudicated results for stroke events from the estrogen-alone substudy, after an average follow-up of 7.1 years, reported no significant differences in distribution of stroke subtypes or severity, including fatal strokes, in women receiving

CE-alone compared to placebo. Estrogen-alone increased the risk for ischemic stroke, and this excess risk was present in all subgroups of women examined^2.

Timing of the initiation of estrogen-alone therapy relative to the start of menopause may affect the overall risk benefit profile. The WHI estrogen-alone substudy stratified by age showed in women 50 to 59 years of age a non-significant trend toward reduced risk for CHD [hazard ratio (HR) 0.63 (95 percent CI, 0.36-1.09)] and overall mortality [HR 0.71 (95 percent CI, 0.46–1.11)].

WHI Estrogen Plus Progestin Substudy

The WHI estrogen plus progestin substudy was also stopped early. According to the predefined stopping rule, after an average follow-up of 5.6 years of treatment, the increased risk of breast cancer and cardiovascular events exceeded the specified benefits included in the “global index.” The absolute excess risk of events included in the “global index” was 19 per 10,000 women-years.

For those outcomes included in the WHI “global index” that reached statistical significance after 5.6 years of follow-up, the absolute excess risks per 10,000 women-years in the group treated with CE plus MPA were 7 more CHD events, 8 more strokes, 10 more PE s, and 8 more invasive breast cancers, while the absolute risk reductions per 10,000 women-years were 6 fewer colorectal cancers and 5 fewer hip fractures.

Results of the CE plus MPA substudy, which included 16,608 women (average 63 years of age, range 50 to 79; 83.9 percent White, 6.8 percent Black, 5.4 percent Hispanic, 3.9 percent Other), are presented in Table 2. These results reflect centrally adjudicated data after an average follow-up of 5.6 years.

TABLE 2 - Relative and Absolute Risk Seen in the Estrogen Plus Progestin Substudy of WHI at an Average of 5.6 Yearsa,b
Event | Relative Risk; CE/MPA vs. Placebo; (95% nCIc) | CE/MPA; n = 8,506 | Placebo; n = 8,102
Event | Relative Risk; CE/MPA vs. Placebo; (95% nCIc) | Absolute Risk per 10,000 Women-Years
CHD events | 1.23 (0.99-1.53) | 41 | 34
Non-fatal MI | 1.28 (1.00-1.63) | 31 | 25
CHD death | 1.10 (0.70-1.75) | 8 | 8
All Strokes | 1.31 (1.03-1.68) | 33 | 25
Ischemic stroke | 144 (1.09-1.90) | 26 | 18
Deep vein thrombosisd | 1.95 (1.43-2.67) | 26 | 13
Pulmonary embolism | 2.13 (1.45-3.11) | 18 | 8
Invasive breast cancere | 1.24 (1.01-1.54) | 41 | 33
Colorectal cancer | 0.61 (0.42-0.87) | 10 | 16
Endometrial cancerd | 0.81 (0.48-1.36) | 6 | 7
Cervical cancerd | 1.44 (0.47-4.42) | 2 | 1
Hip fracture | 0.67 (0.47-0.96) | 11 | 16
Vertebral fracturesd | 0.65 (0.46-0.92) | 11 | 17
Lower arm/wrist fracturesd | 0.71 (0.59-0.85) | 44 | 62
Total fracturesd | 0.76 (0.69-0.83) | 152 | 199
Overall Mortalityf | 1.00 (0.83-1.19) | 52 | 52
Global Indexg | 1.13 (1.02-1.25) | 184 | 165

a Adapted from numerous WHI publications. WHI publications can be viewed at www.nhlbi.nih.gov/whi.

b Results are based on centrally adjudicated data.

c Nominal confidence intervals unadjusted for multiple looks and multiple comparisons.

d Not included in “global index.”

e Includes metastatic and non-metastatic breast cancer, with the exception of in situ cancer.

f All deaths, except from breast or colorectal cancer, definite or probable CHD, PE or cerebrovascular disease.

g A subset of the events was combined in a “global index” defined as the earliest occurrence of CHD events, invasive breast cancer, stroke, pulmonary embolism, colorectal cancer, hip fracture, or death due to other causes.

Timing of the initiation of estrogen plus progestin therapy relative to the start of menopause may affect the overall risk benefit profile. The WHI estrogen plus progestin substudy stratified by age showed in women 50 to 59 years of age, a non-significant trend toward reduced risk for overall mortality [HR 0.69 (95 percent CI, 0.44-1.07)].

Women’s Health Initiative Memory Study

The WHIMS estrogen-alone ancillary study of WHI enrolled 2,947 predominantly healthy hysterectomized postmenopausal women 65 to 79 years of age and older (45 percent were 65 to 69 years of age; 36 percent were 70 to 74 years of age; 19 percent were 75 years of age and older) to evaluate the effects of daily CE (0.625 mg)-alone on the incidence of probable dementia (primary outcome) compared to placebo.

After an average follow-up of 5.2 years, the relative risk of probable dementia for CE-alone versus placebo was 1.49 (95 percent CI, 0.83-2.66). The absolute risk of probable dementia for CE-alone versus placebo was 37 versus 25 cases per 10,000 women-years. Probable dementia as defined in this study included Alzheimer’s disease (AD), vascular dementia (VaD) and mixed types (having features of both AD and VaD). The most common classification of probable dementia in the treatment group and the placebo group was AD. Since the ancillary study was conducted in women 65 to 79 years of age, it is unknown whether these findings apply to younger postmenopausal women [see BOXED WARNINGS, WARNINGS, Probable Dementia and PRECAUTIONS, Geriatric Use].

The WHIMS estrogen plus progestin ancillary study of WHI enrolled 4,532 predominantly healthy postmenopausal women 65 years of age and older (47 percent were 65 to 69 years of age; 35 percent were 70 to 74 years; 18 percent were 75 years of age and older) to evaluate the effects of daily CE (0.625 mg) plus MPA (2.5 mg) on the incidence of probable dementia (primary outcome) compared to placebo.

After an average follow-up of 4 years, the relative risk of probable dementia for CE plus MPA versus placebo was 2.05 (95 percent CI, 1.21-3.48). The absolute risk of probable dementia for CE plus MPA versus placebo was 45 versus 22 per 10,000 women-years. Probable dementia as defined in this study included AD, VaD and mixed types (having features of both AD and VaD). The most common classification of probable dementia in the treatment group and the placebo group was AD. Since the ancillary study was conducted in women 65 to 79 years of age, it is unknown whether these findings apply to younger postmenopausal women [see WARNINGS, Probable Dementia and PRECAUTIONS, Geriatric Use].

When data from the two populations were pooled as planned in the WHIMS protocol, the reported overall relative risk for probable dementia was 1.76 (95 percent CI, 1.19-2.60). Differences between groups became apparent in the first year of treatment. It is unknown whether these findings apply to younger postmenopausal women [see WARNINGS, Probable Dementia and PRECAUTIONS, Geriatric Use].

INDICATIONS AND USAGE

Estradiol Vaginal Cream, 0.01% is indicated in the treatment of moderate to severe symptoms of vulvar and vaginal atrophy due to menopause.

CONTRAINDICATIONS

Estradiol Vaginal Cream, 0.01% should not be used in women with any of the following conditions:

1. Undiagnosed abnormal genital bleeding.
2. Known, suspected, or history of cancer of the breast.
3. Known or suspected estrogen-dependent neoplasia.
4. Active DVT, PE or history of these conditions.
5. Active arterial thromboembolic disease (for example, stroke, MI) or a history of these conditions.
6. Known anaphylactic reaction or angioedema to Estradiol Vaginal Cream, 0.01%.
7. Known liver dysfunction or disease.
8. Known protein C, protein S, or antithrombin deficiency, or other known thrombophilic disorders.
9. Known or suspected pregnancy.

WARNINGS

See BOXED WARNINGS.

Systemic absorption may occur with the use of Estradiol Vaginal Cream USP, 0.01%. The warnings, precautions, and adverse reactions associated with oral estrogen treatment should be taken into account.

1. Cardiovascular disorders

An increased risk of stroke and DVT has been reported with estrogen-alone therapy. An increased risk of PE, DVT, stroke and MI has been reported with estrogen plus progestin therapy. Should any of these occur or be suspected, estrogen with or without progestin therapy should be discontinued immediately.

Risk factors for arterial vascular disease (e.g., hypertension, diabetes mellitus, tobacco use, hypercholesterolemia, and obesity) and/or venous thromboembolism (VTE) (e.g., personal history or family history of VTE, obesity, and systemic lupus erythematosus) should be managed appropriately.

1. Stroke

In the WHI estrogen-alone substudy, a statistically significant increased risk of stroke was reported in women 50 to 79 years of age receiving daily CE (0.625 mg)-alone compared to women in the same age group receiving placebo (45 versus 33 per 10,000 women-years). The increase in risk was demonstrated in year one and persisted [see CLINICAL STUDIES].

Should a stroke occur or be suspected, estrogen-alone therapy should be discontinued immediately.

Subgroup analyses of women 50 to 59 years of age suggest no increased risk of stroke for those women receiving CE (0.625 mg)-alone versus those receiving placebo (18 versus 21 per 10,000 women-years)^3.

In the WHI estrogen plus progestin substudy, a statistically significant increased risk of stroke was reported in women 50 to 79 years of age receiving daily CE (0.625 mg) plus MPA (2.5 mg) compared to women in the same age group receiving placebo (33 versus 25 per 10,000 women-years) [see CLINICAL STUDIES]. The increase in risk was demonstrated after the first year and persisted^3. Should a stroke occur or be suspected, estrogen plus progestin therapy should be discontinued immediately.

1. Coronary Heart Disease

In the WHI estrogen-alone substudy, no overall effect on coronary heart disease (CHD) events (defined as nonfatal MI, silent MI and CHD death) was reported in women receiving estrogen-alone compared to placebo^4 [see CLINICAL STUDIES].

Subgroup analyses of women 50 to 59 years of age suggest a statistically non-significant reduction in CHD events (CE [0.625 mg]-alone compared to placebo) in women with less than 10 years since menopause (8 versus 16 per 10,000 women-years)^3.

In the WHI estrogen plus progestin substudy, there was a statistically non-significant increased risk of CHD events reported in women receiving daily CE (0.625 mg) plus MPA (2.5 mg) compared to women receiving placebo (41 versus 34 per 10,000 women-years)^3. An increase in relative risk was demonstrated in year 1, and a trend toward decreasing relative risk was reported in years 2 through 5 [see CLINICAL STUDIES].

In postmenopausal women with documented heart disease (n = 2,763), average age 66.7 years of age, in a controlled clinical trial of secondary prevention of cardiovascular disease (Heart and Estrogen/Progestin Replacement Study; HERS), treatment with daily CE (0.625 mg) plus MPA (2.5 mg) demonstrated no cardiovascular benefit. During an average follow-up of 4.1 years, treatment with CE plus MPA did not reduce the overall rate of CHD events in postmenopausal women with established coronary heart disease. There were more CHD events in the CE plus MPA-treated group than in the placebo group in year 1, but not during the subsequent years. Two thousand, three hundred and twenty one (2,321) women from the original HERS trial agreed to participate in an open label extension of HERS, HERS II. Average follow-up in HERS II was an additional 2.7 years, for a total of 6.8 years overall. Rates of CHD events were comparable among women in the CE plus MPA group and the placebo group in HERS, HERS II, and overall.

1. Venous Thromboembolism

In the WHI estrogen-alone substudy, the risk of VTE (DVT and PE) was increased for women receiving daily CE (0.625 mg)-alone compared to women receiving placebo (30 versus 22 per 10,000 women-years), although only the increased risk of DVT reached statistical significance (23 versus 15 per 10,000 women-years). The increase in VTE risk was demonstrated during the first 2 years^5 [see CLINICAL STUDIES]. Should a VTE occur or be suspected, estrogen-alone therapy should be discontinued immediately.

In the WHI estrogen plus progestin substudy, a statistically significant 2-fold greater rate of VTE was reported in women receiving daily CE (0.625 mg) plus MPA (2.5 mg) compared to women receiving placebo (35 versus 17 per 10,000 women-years). Statistically significant increases in risk for both DVT (26 versus 13 per 10,000 women-years) and PE (18 versus 8 per 10,000 women-years) were also demonstrated. The increase in VTE risk was observed during the first year and persisted^6 [see CLINICAL STUDIES]. Should a VTE occur or be suspected, estrogen plus progestin therapy should be discontinued immediately.

If feasible, estrogens should be discontinued at least 4 to 6 weeks before surgery of the type associated with an increased risk of thromboembolism, or during periods of prolonged immobilization.

2. Malignant Neoplasms

1. Endometrial Cancer

An increased risk of endometrial cancer has been reported with the use of unopposed estrogen therapy in a woman with a uterus. The reported endometrial cancer risk among unopposed estrogen users is about 2- to 12-times greater than in non-users, and appears dependent on duration of treatment and on estrogen dose. Most studies show no significant increased risk associated with use of estrogens for less than one year. The greatest risk appears associated with prolonged use, with increased risks of 15- to 24-fold for five to ten years or more and this risk has been shown to persist for at least 8 to 15 years after estrogen therapy is discontinued.

Clinical surveillance of all women using estrogen-alone or estrogen plus progestin therapy is important. Adequate diagnostic measures, including directed or random endometrial sampling when indicated, should be undertaken to rule out malignancy in postmenopausal women with undiagnosed persistent or recurring abnormal genital bleeding.

There is no evidence that the use of natural estrogens results in a different endometrial risk profile than synthetic estrogens of equivalent estrogen dose. Adding a progestin to estrogen therapy has been shown to reduce the risk of endometrial hyperplasia, which may be a precursor to endometrial cancer.

1. Breast Cancer

The most important randomized clinical trial providing information about breast cancer in estrogen-alone users is the WHI substudy of daily CE (0.625 mg)-alone. In the WHI estrogen-alone substudy, after an average follow-up of 7.1 years, daily CE (0.625 mg)-alone was not associated with an increased risk of invasive breast cancer (relative risk [RR] 0.80)^7 [see CLINICAL STUDIES].

The most important randomized clinical trial providing information about breast cancer in estrogen plus progestin users is the WHI substudy of daily CE (0.625 mg) plus MPA (2.5 mg). After a mean follow-up of 5.6 years, the estrogen plus progestin substudy reported an increased risk of invasive breast cancer in women who took daily CE plus MPA. In this substudy, prior use of estrogen-alone or estrogen plus progestin therapy was reported by 26 percent of the women. The relative risk of invasive breast cancer was 1.24, and the absolute risk was 41 versus 33 cases per 10,000 women-years, for CE plus MPA compared with placebo. Among women who reported prior use of hormone therapy, the relative risk of invasive breast cancer was 1.86, and the absolute risk was 46 versus 25 cases per 10,000 women-years, for CE plus MPA compared with placebo. Among women who reported no prior use of hormone therapy, the relative risk of invasive breast cancer was 1.09, and the absolute risk was 40 versus 36 cases per 10,000 women-years, for CE plus MPA compared with placebo. In the same substudy, invasive breast cancers were larger, were more likely to be node positive, and were diagnosed at a more advanced stage in the CE (0.625 mg) plus MPA (2.5 mg) group compared with the placebo group. Metastatic disease was rare with no apparent difference between the two groups. Other prognostic factors such as histologic subtype, grade and hormone receptor status did not differ between the groups^8 [see CLINICAL STUDIES].

Consistent with the WHI clinical trial, observational studies have also reported an increased risk of breast cancer for estrogen plus progestin therapy, and a smaller increased risk for estrogen-alone therapy, after several years of use. One large meta-analysis of prospective cohort studies reported increased risks that were dependent upon duration of use and could last up to >10 years after discontinuation of estrogen plus progestin therapy and estrogen-alone therapy. Extension of the WHI trials also demonstrated increased breast cancer risk associated with estrogen plus progestin therapy. Observational studies also suggest that the risk of breast cancer was greater, and became apparent earlier, with estrogen plus progestin therapy as compared to estrogen-alone therapy. However, these studies have not generally found significant variation in the risk of breast cancer among different estrogen plus progestin combinations, doses, or routes of administration.

The use of estrogen-alone and estrogen plus progestin therapy has been reported to result in an increase in abnormal mammograms requiring further evaluation.

All women should receive yearly breast examinations by a healthcare provider and perform monthly breast self-examinations. In addition, mammography examinations should be scheduled based on patient age, risk factors, and prior mammogram results.

1. Ovarian Cancer

The WHI estrogen plus progestin substudy reported a statistically non-significant increased risk of ovarian cancer. After an average follow-up of 5.6 years, the relative risk for ovarian cancer for CE plus MPA versus placebo was 1.58 (95 percent CI, 0.77-3.24). The absolute risk for CE plus MPA was 4 versus 3 cases per 10,000 women-years^9. In some epidemiologic studies, the use of estrogen plus progestin and estrogen-only products, in particular for 5 or more years, has been associated with an increased risk of ovarian cancer. However, the duration of exposure associated with increased risk is not consistent across all epidemiologic studies, and some report no association.

3. Probable Dementia

In the WHIMS estrogen-alone ancillary study of WHI, a population of 2,947 hysterectomized women 65 to 79 years of age was randomized to daily CE (0.625 mg)-alone or placebo.

After an average follow-up of 5.2 years, 28 women in the estrogen-alone group and 19 women in the placebo group were diagnosed with probable dementia. The relative risk of probable dementia for CE-alone versus placebo was 1.49 (95 percent CI, 0.83-2.66). The absolute risk of probable dementia for CE-alone versus placebo was 37 versus 25 cases per 10,000 women-years^10 [see CLINICAL STUDIES and PRECAUTIONS, Geriatric Use].

In the WHIMS estrogen plus progestin ancillary study, a population of 4,532 postmenopausal women 65 to 79 years of age was randomized to daily CE (0.625 mg) plus MPA (2.5 mg) or placebo.

After an average follow-up of 4 years, 40 women in the CE plus MPA group and 21 women in the placebo group were diagnosed with probable dementia. The relative risk of probable dementia for CE plus MPA versus placebo was 2.05 (95 percent CI, 1.21-3.48). The absolute risk of probable dementia for CE plus MPA versus placebo was 45 versus 22 cases per 10,000 women-years^10 [see CLINICAL STUDIES and PRECAUTIONS, Geriatric Use].

When data from the two populations in the WHIMS estrogen-alone and estrogen plus progestin ancillary studies were pooled as planned in the WHIMS protocol, the reported overall relative risk for probable dementia was 1.76 (95 percent CI, 1.19-2.60). Since both ancillary studies were conducted in women 65 to 79 years of age, it is unknown whether these findings apply to younger postmenopausal women^10 [see PRECAUTIONS, Geriatric Use].

4. Gallbladder Disease

A 2- to 4-fold increase in the risk of gallbladder disease requiring surgery in postmenopausal women receiving estrogens has been reported.

5. Hypercalcemia

Estrogen administration may lead to severe hypercalcemia in patients with breast cancer and bone metastases.

If hypercalcemia occurs, use of the drug should be stopped and appropriate measures taken to reduce the serum calcium level.

6. Visual Abnormalities

Retinal vascular thrombosis has been reported in patients receiving estrogens. Discontinue medication pending examination if there is sudden partial or complete loss of vision, or a sudden onset of proptosis, diplopia, or migraine. If examination reveals papilledema or retinal vascular lesions, estrogens should be permanently discontinued.

7. Anaphylactic Reaction and Angioedema

Cases of anaphylaxis, which develop within minutes to hours after taking orally-administered estrogen and require emergency medical management, have been reported in the postmarketing setting. Skin (hives, pruritis, swollen lips-tongue-face) and either respiratory tract (respiratory compromise) or gastrointestinal tract (abdominal pain, vomiting) involvement has been noted.

Angioedema involving the tongue, larynx, face, hands and feet requiring medical intervention has occurred postmarketing in patients taking orally-administered estrogen. If angioedema involves the tongue, glottis, or larynx, airway obstruction may occur. Patients who develop an anaphylactic reaction with or without angioedema after treatment with oral estrogen should not receive oral estrogen again.

8. Hereditary Angioedema

Exogenous estrogens may exacerbate symptoms of angioedema in women with hereditary angioedema.

PRECAUTIONS

A. General

1. Addition of a Progestin When a Woman Has Not Had a Hysterectomy

Studies of the addition of a progestin for 10 or more days of a cycle of estrogen administration, or daily with estrogen in a continuous regimen, have reported a lowered incidence of endometrial hyperplasia than would be induced by estrogen treatment alone. Endometrial hyperplasia may be a precursor to endometrial cancer.

There are, however, possible risks that may be associated with the use of progestins with estrogens compared to estrogen-alone regimens. These include a possible increased risk of breast cancer.

1. Elevated Blood Pressure

In a small number of case reports, substantial increases in blood pressure have been attributed to idiosyncratic reactions to estrogens. In a large, randomized, placebo-controlled clinical trial, a generalized effect of estrogens on blood pressure was not seen.

1. Hypertriglyceridemia

In women with pre-existing hypertriglyceridemia, estrogen therapy may be associated with elevations of plasma triglycerides leading to pancreatitis and other complications. Consider discontinuation of treatment if pancreatitis occurs.

1. Hepatic Impairment and/or Past History of Cholestatic Jaundice

Estrogens may be poorly metabolized in patients with impaired liver function. For women with a history of cholestatic jaundice associated with past estrogen use or with pregnancy, caution should be exercised and in the case of recurrence, medication should be discontinued.

1. Hypothyroidism

Estrogen administration leads to increased thyroid-binding globulin (TBG) levels. Women with normal thyroid function can compensate for the increased TBG by making more thyroid hormone, thus maintaining free T4 and T3 serum concentrations in the normal range. Women dependent on thyroid hormone replacement therapy who are also receiving estrogens may require increased doses of their thyroid replacement therapy. These women should have their thyroid function monitored in order to maintain their free thyroid hormone levels in an acceptable range.

1. Fluid Retention

Estrogens may cause some degree of fluid retention. Women with conditions that might be influenced by this factor, such as a cardiac or renal dysfunction, warrant careful observation when estrogen-alone is prescribed.

1. Hypocalcemia

Estrogen therapy should be used with caution in women with hypoparathyroidism as estrogen-induced hypocalcemia may occur.

1. Exacerbation of Endometriosis

A few cases of malignant transformation of residual endometrial implants have been reported in women treated post-hysterectomy with estrogen alone therapy. For patients known to have residual endometriosis post-hysterectomy, the addition of progestin should be considered.

1. Exacerbation of Other Conditions

Estrogen therapy may cause an exacerbation of asthma, diabetes mellitus, epilepsy, migraine or porphyria, systemic lupus erythematosus, and hepatic hemangiomas and should be used with caution in women with these conditions.

B. Patient Information

Physicians are advised to discuss the PATIENT INFORMATION leaflet with women for whom they prescribe Estradiol Vaginal Cream, 0.01%.

C. Laboratory Tests

Serum FSH and estradiol levels have not been shown to be useful in the management of moderate to severe symptoms of vulvar and vaginal atrophy.

D. Drug-Laboratory Test Interactions

1. Accelerated prothrombin time, partial thromboplastin time, and platelet aggregation time; increased platelet count; increased factors II, VII antigen, VIII antigen, VIII coagulant activity, IX, X, XII, VII-X complex, II-VII-X complex, and beta-thromboglobulin; decreased levels of anti-factor Xa and antithrombin III, decreased antithrombin III activity; increased levels of fibrinogen and fibrinogen activity; increased plasminogen antigen and activity.
2. Increased thyroid-binding globulin (TBG) leading to increased circulating total thyroid hormone levels, as measured by protein-bound iodine (PBI), T4 levels (by column or by radioimmunoassay) or T3 levels by radioimmunoassay. T3 resin uptake is decreased, reflecting the elevated TBG. Free T4 and free T3 concentrations are unaltered. Women on thyroid replacement therapy may require higher dose of thyroid hormone.
3. Other binding proteins may be elevated in serum, i.e., corticosteroid binding globulin (CBG), sex hormone-binding globulin (SHBG), leading to increased total circulating corticosteroids and sex steroids, respectively. Free hormone concentrations, such as testosterone and estradiol, may be decreased. Other plasma proteins may be increased (angiotensinogen/renin substrate, alpha-1-antitrypsin, ceruloplasmin).
4. Increased plasma high-density lipoprotein (HDL) and HDL2 cholesterol subfraction concentrations, reduced low-density lipoprotein (LDL) cholesterol concentration, increased triglycerides levels.
5. Impaired glucose tolerance.

E. CARCINOGENESIS, MUTAGENESIS, IMPAIRMENT OF FERTILITY

Long-term continuous administration of estrogen, with and without progestin, in women with and without a uterus, has shown an increased risk of endometrial cancer, breast cancer, and ovarian cancer. (See BOXED WARNINGS, WARNINGS and PRECAUTIONS.)

Long term continuous administration of natural and synthetic estrogens in certain animal species increases the frequency of carcinomas of the breast, uterus, cervix, vagina, testis, and liver.

F. Pregnancy

Estradiol Vaginal Cream, 0.01% should not be used during pregnancy [see CONTRAINDICATIONS].

There appears to be little or no increased risk of birth defects in children born to women who have used estrogens and progestins as an oral contraceptive inadvertently during early pregnancy.

G. Nursing Mothers

Estradiol Vaginal Cream, 0.01% should not be used during lactation. Estrogen administration to nursing women has been shown to decrease the quantity and quality of the breast milk. Detectable amounts of estrogens have been identified in the milk of women receiving estrogen therapy. Caution should be exercised when Estradiol Vaginal Cream, 0.01% is administered to a nursing woman.

H. Pediatric Use

Estradiol Vaginal Cream, 0.01% work out is not indicated in children. Clinical studies have not been conducted in the pediatric population.

I. Geriatric Use

There have not been sufficient numbers of geriatric patients involved in studies utilizing Estradiol Vaginal Cream, 0.01% to determine whether those over 65 years of age differ from younger subjects in their response to Estradiol Vaginal Cream, 0.01%.

The Women’s Health Initiative Study

In the WHI estrogen-alone substudy (daily CE [0.625 mg]-alone versus placebo), there was a higher relative risk of stroke in women greater than 65 years of age [see CLINICAL STUDIES and WARNINGS].

In the WHI estrogen plus progestin substudy (daily CE [0.625 mg] plus MPA [2.5 mg] versus placebo), there was a higher relative risk of nonfatal stroke and invasive breast cancer in women greater than 65 years of age [see CLINICAL STUDIES and WARNINGS].

The Women’s Health Initiative Memory Study

In the WHIMS ancillary studies of postmenopausal women 65 to 79 years of age, there was an increased risk of developing probable dementia in women receiving estrogen-alone or estrogen plus progestin when compared to placebo [see CLINICAL STUDIES and WARNINGS].

Since both ancillary studies were conducted in women 65 to 79 years of age, it is unknown whether these findings apply to younger postmenopausal women^10 [see CLINICAL STUDIES and WARNINGS].

ADVERSE REACTIONS

See BOXED WARNINGS, WARNINGS and PRECAUTIONS.

Systemic absorption may occur with the use of Estradiol Vaginal Cream, 0.01%. The warnings, precautions, and adverse reactions associated with oral estrogen treatment should be taken into account.

The following adverse reactions have been reported with estrogen and/or progestin therapy.

1. Genitourinary System

Abnormal uterine bleeding or spotting; dysmenorrhea or pelvic pain, increase in size of uterine leiomyomata; vaginitis, including vaginal candidiasis; change in cervical secretion; cystitis-like syndrome; application site reactions of vulvovaginal discomfort including burning and irritation; genital pruritus; ovarian cancer; endometrial hyperplasia; endometrial cancer.

2. Breasts

Tenderness, enlargement, pain, nipple discharge, fibrocystic breast changes; breast cancer.

3. Cardiovascular

Deep and superficial venous thrombosis; pulmonary embolism; myocardial infarction; stroke; increase in blood pressure.

4. Gastrointestinal

Nausea, vomiting; abdominal cramps, bloating; increased incidence of gallbladder disease.

5. Skin

Chloasma that may persist when drug is discontinued; loss of scalp hair; hirsutism; rash.

6. Eyes

Retinal vascular thrombosis, intolerance to contact lenses.

7. Central Nervous System

Headache; migraine; dizziness; mental depression; nervousness; mood disturbances; irritability; dementia.

8. Miscellaneous

Increase or decrease in weight; glucose intolerance; edema; arthralgias; leg cramps; changes in libido; urticaria; exacerbation of asthma; increased triglycerides; hypersensitivity (including erythema multiforme).

OVERDOSAGE

Overdosage of estrogen may cause nausea, vomiting, breast tenderness, abdominal pain, drowsiness and fatigue, and withdrawal bleeding may occur in women. Treatment of overdose consists of discontinuation of Estradiol Vaginal Cream, 0.01% therapy together with institution of appropriate symptomatic care.

DOSAGE AND ADMINISTRATION

Use of Estradiol Vaginal Cream, 0.01% alone or in combination with a progestin, should be limited to the shortest duration consistent with treatment goals and risks for the individual woman. Postmenopausal women should reevaluate periodically as clinically appropriate to determine if treatment is still necessary. For treatment of vulvar and vaginal atrophy associated with the menopause, the lowest dose and regimen that will control symptoms should be chosen and medication should be discontinued as promptly as possible. For women who have a uterus, adequate diagnostic measures, including directed and random endometrial sampling when indicated, should be undertaken to rule out malignancy in cases of undiagnosed persistent or recurring abnormal genital bleeding.

Usual Dosage: The usual dosage range is 2 to 4 g (marked on the applicator) daily for one or two weeks, then gradually reduced to one half initial dosage for a similar period. A maintenance dosage of 1 g, one to three times a week, may be used after restoration of the vaginal mucosa has been achieved.

NOTE: The number of doses per tube will vary with dosage requirements and patient handling.

HOW SUPPLIED

Estradiol Vaginal Cream USP, 0.01%

NDC 42291-426-42: Tube containing 1½ oz (42.5 g) with a calibrated plastic applicator for delivery of 1, 2, 3, or 4 g.

Store at room temperature 20° to 25°C (59° to 77°F). Protect from temperatures in excess of 40°C (104°F).

Keep Estradiol Vaginal Cream, 0.01% out of the reach of children.

REFERENCES

1. Jackson RD, et al. Effects of Conjugated Equine Estrogen on Risk of Fractures and BMD in Postmenopausal Women With Hysterectomy: Results From the Women’s Health Initiative Randomized Trial. J Bone Miner Res. 2006;21:817-828.
2. Hendrix SL, et al. Effects of Conjugated Equine Estrogen on Stroke in the Women’s Health Initiative. Circulation. 2006;113:2425-2434.
3. Rossouw JE, et al. Postmenopausal Hormone Therapy and Risk of Cardiovascular Disease by Age and Years Since Menopause. JAMA. 2007;297:1465-1477.
4. Hsia J, et al. Conjugated Equine Estrogens and Coronary Heart Disease. Arch Int Med. 2006;166:357-365.
5. Curb JD, et al. Venous Thrombosis and Conjugated Equine Estrogen in Women Without a Uterus. Arch Int Med. 2006;166:772-780.
6. Cushman M, et al. Estrogen Plus Progestin and Risk of Venous Thrombosis. JAMA. 2004;292:1573-1580.
7. Stefanick ML, et al. Effects of Conjugated Equine Estrogens on Breast Cancer and Mammography Screening in Postmenopausal Women With Hysterectomy. JAMA. 2006;295:1647-1657.
8. Chlebowski RT, et al. Influence of Estrogen Plus Progestin on Breast Cancer and Mammography in Healthy Postmenopausal Women. JAMA. 2003;289:3234-3253.
9. Anderson GL, et al. Effects of Estrogen Plus Progestin on Gynecologic Cancers and Associated Diagnostic Procedures. JAMA. 2003;290:1739-1748.
10. Shumaker SA, et al. Conjugated Equine Estrogens and Incidence of Probable Dementia and Mild Cognitive Impairment in Postmenopausal Women. JAMA. 2004;291:2947-2958.

Distributed By AvKARE

Pulaski, TN 38478

Manufactured By Padagis

Yeruham, Israel

Rev 11-23

4H7G5 JP T3

INFORMATION FOR THE PATIENT

Read this PATIENT INFORMATION before you start using Estradiol Vaginal Cream, 0.01% and read what you get each time you refill your Estradiol Vaginal Cream, 0.01% prescription. There may be new information. This information does not take the place of talking with your healthcare provider about your menopausal symptoms or your treatment.

What is the most important information I should know about Estradiol Vaginal Cream, 0.01% (an estrogen hormone)?

- Using estrogen-alone may increase your chance of getting cancer of the uterus (womb). Report any unusual vaginal bleeding right away while you are using Estradiol Vaginal Cream, 0.01%. Vaginal bleeding after menopause may be a warning sign of cancer of the uterus (womb). Your healthcare provider should check any unusual vaginal bleeding to find out the cause.
- Do not use estrogen-alone to prevent heart disease, heart attacks, strokes or dementia (decline in brain function)
- Using estrogen-alone may increase your chances of getting strokes or blood clots
- Using estrogen-alone may increase your chance of getting dementia, based on a study of women age 65 years of age or older
- Do not use estrogens with progestins to prevent heart disease, heart attacks, strokes or dementia
- Using estrogens with progestins may increase your chances of getting heart attacks, strokes, breast cancer, or blood clots
- Using estrogens with progestins may increase your chance of getting dementia, based on a study of women age 65 years of age or older
- You and your healthcare provider should talk regularly about whether you still need treatment with Estradiol Vaginal Cream, 0.01%

What is Estradiol Vaginal Cream, 0.01%?

Estradiol Vaginal Cream, 0.01% is a medicine that contains an estrogen hormone.

What is Estradiol Vaginal Cream, 0.01% used for? Estradiol Vaginal Cream, 0.01% is used after menopause to:

- Treat moderate to severe menopausal changes in and around the vagina

You and your healthcare provider should talk regularly about whether you still need treatment with Estradiol Vaginal Cream, 0.01% to control these problems.

Who should not use Estradiol Vaginal Cream, 0.01%?

Do not start using Estradiol Vaginal Cream, 0.01% if you:

- Have unusual vaginal bleeding
- Currently have or have had certain cancers

Estrogens may increase the chances of getting certain types of cancers, including cancer of the breast or uterus. If you have or have had cancer, talk with your healthcare provider about whether you should use Estradiol Vaginal Cream, 0.01%.

- Had a stroke or heart attack
- Currently have or have had blood clots
- Currently have or have had liver problems
- Have been diagnosed with a bleeding disorder
- Are allergic to Estradiol Vaginal Cream, 0.01% or any of its ingredients

See the list of ingredients in Estradiol Vaginal Cream, 0.01% at the end of this leaflet.

- Think you may be pregnant

Tell your healthcare provider:

- If you have unusual vaginal bleeding

Vaginal bleeding after menopause may be a warning sign of cancer of the uterus (womb). Your healthcare provider should check any unusual vaginal bleeding to find out the cause.

- About all of your medical problems

Your healthcare provider may need to check you more carefully if you have certain conditions, such as asthma (wheezing), epilepsy (seizures), diabetes, migraine, endometriosis, lupus, problems with your heart, liver, thyroid, kidneys, or have high calcium levels in your blood.

- About all the medicines you take

This includes prescription and nonprescription medicines, vitamins, and herbal supplements. Some medicines may affect how Estradiol Vaginal Cream, 0.01% works.

Estradiol Vaginal Cream, 0.01% may also affect how your other medicines work.

- If you are going to have surgery or will be on bed rest.

You may need to stop using Estradiol Vaginal Cream, 0.01%.

- If you are breastfeeding

The estrogen hormone in Estradiol Vaginal Cream, 0.01% can pass into your breast milk.

How should I use Estradiol Vaginal Cream, 0.01%?

Estradiol Vaginal Cream, 0.01% is a cream that you place in your vagina with the applicator provided with the cream.

- Take the dose recommended by your healthcare provider and talk to him or her about how well that dose is working for you
- Estrogens should be used at the lowest dose possible for your treatment only as long as needed. You and your healthcare provider should talk regularly (for example, every 3 to 6 months) about the dose you are using and whether you still need treatment with Estradiol Vaginal Cream, 0.01%
- Step 1. Remove the cap from the tube. (There is no seal on tube)
- Step 2. Do not separate plunger from applicator.
- Step 3. Screw threaded end of applicator onto the open tube until secure.
- Step 4. Position upright in order to view the calibrated gram amounts.
- Step 5. Gently squeeze tube from the bottom to expel the prescribed amount of
- Estradiol Vaginal Cream, 0.01% into the applicator. As cream is squeezed out, plunger will rise to indicate amount of grams.
- Step 6. Unscrew applicator from tube.
- Step 7. Replace cap on tube.
- Step 8. Lie on back with knees drawn up. To deliver medication, gently insert applicator deeply into vagina and press plunger downward to its original position.
- Step 9. To cleanse applicator: Pull plunger to remove it from barrel. Wash with mild soap and warm water (DO NOT BOIL OR USE HOT WATER)

What are the possible side effects of Estradiol Vaginal Cream, 0.01%

Although Estradiol Vaginal Cream, 0.01% is only used in and around the vagina, the risks associated with oral estrogens should be taken into account.

Side effects are grouped by how serious they are and how often they happen when you are treated.

Serious, but less common side effects include:

- Heart attack
- Stroke
- Blood clots
- Dementia
- Breast cancer
- Cancer of the lining of the uterus (womb)
- Cancer of the ovary
- High blood pressure
- High blood sugar
- Gallbladder disease
- Liver problems
- Enlargement of benign tumors of the uterus (“fibroids”)
- Severe allergic reaction

Call your healthcare provider right away if you get any of the following warning signs or any other unusual symptoms that concern you:

- New breast lumps
- Unusual vaginal bleeding
- Changes in vision or speech
- Sudden new severe headaches
- Severe pains in your chest or legs with or without shortness of breath, weakness and fatigue
- Swollen lips, tongue or face

Less serious, but common side effects include:

- Headache
- Breast pain
- Irregular vaginal bleeding or spotting
- Stomach or abdominal cramps, bloating
- Nausea and vomiting
- Hair loss
- Fluid retention
- Vaginal yeast infection
- Reactions from inserting Estradiol Vaginal Cream, 0.01%, such as vaginal burning,
- irritation, and itching

These are not all the possible side effects of Estradiol Vaginal Cream, 0.01%. For more information, ask your healthcare provider or pharmacist for advice about side effects.

You may report side effects to FDA at 1-800-FDA-1088.

What can I do to lower my chances of a serious side effect with Estradiol Vaginal Cream, 0.01%?

- Talk with your healthcare provider regularly about whether you should continue using Estradiol Vaginal Cream, 0.01%.
- If you have a uterus, talk with your healthcare provider about whether the addition of a progestin is right for you. The addition of a progestin is generally recommended for a woman with a uterus to reduce the chance of getting cancer of the uterus.
- See your healthcare provider right away if you get vaginal bleeding while using Estradiol Vaginal Cream, 0.01%.
- Have a pelvic exam, breast exam and mammogram (breast X-ray) every year unless your healthcare provider tells you something else. If members of your family have had breast cancer or if you have ever had breast lumps or an abnormal mammogram, you may need to have breast exams more often.
- If you have high blood pressure, high cholesterol (fat in the blood), diabetes, are overweight, or if you use tobacco, you may have higher chances for getting heart disease. Ask your healthcare provider for ways to lower your chances for getting heart disease.

General information about safe and effective use of Estradiol Vaginal Cream, 0.01%

Medicines are sometimes prescribed for conditions that are not mentioned in patient information leaflets. Do not use Estradiol Vaginal Cream, 0.01% for conditions for which it was not prescribed. Do not give Estradiol Vaginal Cream, 0.01% to other people, even if they have the same symptoms you have. It may harm them.

Keep Estradiol Vaginal Cream, 0.01% out of the reach of children.

This leaflet provides a summary of the most important information about Estradiol Vaginal Cream, 0.01%. If you would like more information, talk with your healthcare provider or pharmacist. You can ask for information about Estradiol Vaginal Cream, 0.01% that is written for health professionals. You can get more information by calling the toll free number 1-866-634-9120.

What are the ingredients in Estradiol Vaginal Cream, 0.01%?

Each gram of Estradiol Vaginal Cream, 0.01% contains 0.1 mg estradiol in a nonliquefying base containing purified water, propylene glycol, stearyl alcohol, white ceresin wax, mono-and di-glycerides, hypromellose 2208 (4000 cps), sodium lauryl sulfate, methylparaben, edetate di-sodium, tertiary-butylhydroquinone and polysorbate 80.

HOW SUPPLIED

Estradiol Vaginal Cream USP, 0.01%

NDC 42291-426-42: Tube containing 1½ oz (42.5 g) with a calibrated plastic applicator for delivery of 1, 2, 3, or 4 g.

Store at room temperature 20° to 25°C (59° to 77°F). Protect from temperatures in excess of 40°C (104°F).

For more information, you may also contact AvKARE at 1-855-361-3993.

Distributed By AvKARE

Pulaski, TN 38478

Manufactured By Padagis

Yeruham, Israel

Rev 011-23

4H7G5 JP T3